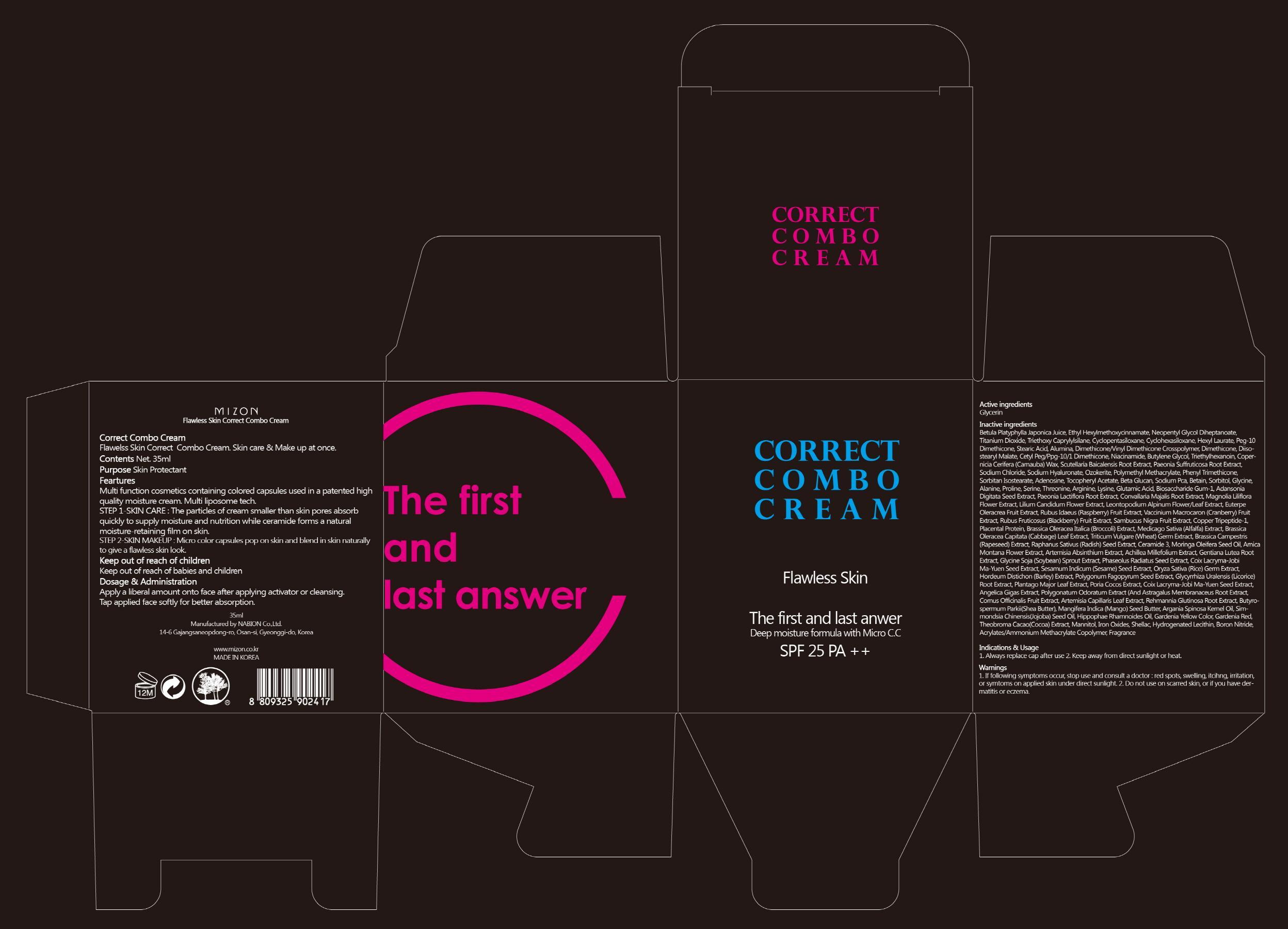 DRUG LABEL: CORRECT COMBO
NDC: 57718-020 | Form: CREAM
Manufacturer: MIZON CO., LTD.
Category: otc | Type: HUMAN OTC DRUG LABEL
Date: 20130503

ACTIVE INGREDIENTS: Glycerin 7 mg/35 mL
INACTIVE INGREDIENTS: NIACINAMIDE; DIMETHICONE; DIISOSTEARYL MALATE

ACTIVE INGREDIENT

Active ingredient: Glycerin 20%

INACTIVE INGREDIENT

Inactive ingredients:
Betula Platyphylla Japonica Juice, Ethyl Hexylmethoxycinnamate, Neopentyl Glycol Diheptanoate, Titanium Dioxide, Triethoxy Caprylylsilane, Cyclopentasiloxane, Cyclohexasiloxane, Hexyl Laurate, Peg-10 Dimethicone, Stearic Acid, Alumina, Dimethicone/Vinyl Dimethicone Crosspolymer, Dimethicone, Diisostearyl Malate, Cetyl Peg/Ppg-10/1 Dimethicone, Niacinamide, Butylene Glycol, Triethylhexanoin, Copernicia Cerifera (Carnauba) Wax, Scutellaria Baicalensis Root Extract, Paeonia Suffruticosa Root Extract, Sodium Chloride, Sodium Hyaluronate, Ozokerite, Polymethyl Methacrylate, Phenyl Trimethicone, Sorbitan Isostearate, Adenosine, Tocopheryl Acetate, Beta Glucan, Sodium Pca, Betain, Sorbitol, Glycine, Alanine, Proline, Serine, Threonine, Arginine, Lysine, Glutamic Acid, Biosaccharide Gum-1, Adansonia Digitata Seed Extract, Paeonia Lactiflora Root Extract, Convallaria Majalis Root Extract, Magnolia Liliflora Flower Extract, Lilium Candidum Flower Extract, Leontopodium Alpinum Flower/Leaf Extract, Euterpe Oleracrea Fruit Extract, Rubus Idaeus (Raspberry) Fruit Extract, Vaccinium Macrocaron (Cranberry) Fruit Extract, Rubus Fruticosus (Blackberry) Fruit Extract, Sambucus Nigra Fruit Extract, Copper Tripeptide-1, Placental Protein, Brassica Oleracea Italica (Broccoli) Extract, Medicago Sativa (Alfalfa) Extract, Brassica Oleracea Capitata (Cabbage) Leaf Extract, Triticum Vulgare (Wheat) Germ Extract, Brassica Campestris (Rapeseed) Extract, Raphanus Sativus (Radish) Seed Extract, Ceramide 3, Moringa Oleifera Seed Oil, Arnica Montana Flower Extract, Artemisia Absinthium Extract, Achillea Millefolium Extract, Gentiana Lutea Root Extract, Glycine Soja (Soybean) Sprout Extract, Phaseolus Radiatus Seed Extract, Coix Lacryma-Jobi Ma-Yuen Seed Extract, Sesamum Indicum (Sesame) Seed Extract, Oryza Sativa (Rice) Germ Extract, Hordeum Distichon (Barley) Extract, Polygonum Fagopyrum Seed Extract, Glycyrrhiza Uralensis (Licorice) Root Extract, Plantago Major Leaf Extract, Poria Cocos Extract, Coix Lacryma-Jobi Ma-Yuen Seed Extract, Angelica Gigas Extract, Polygonatum Odoratum Extract (And Astragalus Membranaceus Root Extract, Cornus Officinalis Fruit Extract, Artemisia Capillaris Leaf Extract, Rehmannia Glutinosa Root Extract, Butyrospermum Parkii(Shea Butter), Mangifera Indica (Mango) Seed Butter, Argania Spinosa Kernel Oil, Simmondsia Chinensis(Jojoba) Seed Oil, Hippophae Rhamnoides Oil, Gardenia Yellow Color, Gardenia Red, Theobroma Cacao(Cocoa) Extract, Mannitol, Iron Oxides, Shellac, Hydrogenated Lecithin, Boron Nitride, Acrylates/Ammonium Methacrylate Copolymer, Fragrance

PURPOSE

Purpose: Skin Protectant

WARNINGS

1. If following symptoms occur, stop use and consult a doctor: red spots, swelling, itcihng, irritation, or symtoms on applied skin under direct sunlight.
2. Do not use on scarred skin, or if you have dermatitis or eczema.

KEEP OUT OF REACH OF CHILDREN

Keep out of reach of babies and children

INDICATIONS AND USAGE

1. Always replace cap after use
2. Keep away from direct sunlight or heat.

DOSAGE AND ADMINISTRATION

Apply a liberal amount onto face after applying activator or cleansing.
Tap applied face softly for better absorption.